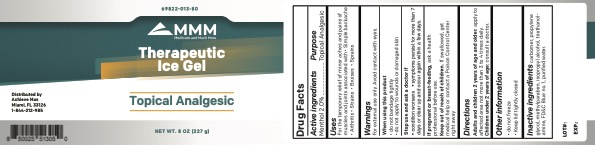 DRUG LABEL: MMM Ice Gel
NDC: 69822-013 | Form: GEL
Manufacturer: Southern Sales & Services, Inc
Category: otc | Type: HUMAN OTC DRUG LABEL
Date: 20210101

ACTIVE INGREDIENTS: MENTHOL, UNSPECIFIED FORM 2 g/100 g
INACTIVE INGREDIENTS: TROLAMINE; METHYLPARABEN; FD&C BLUE NO. 1; CARBOMER HOMOPOLYMER TYPE C; PROPYLENE GLYCOL; ISOPROPYL ALCOHOL; WATER

MMM Therapeutic Ice Gel
Topical Analgesic

Active Ingredients Menthol 2.0% Purpose: Topical Analgesic

PURPOSE

Topical Analgesic

INDICATIONS AND USAGE

For the temporary relief of minor aches and pains of muscles and joints associated with

- Simple backache
- Arthritis
- Strains
- Bruises
- Sprains

WARNINGS

For external use only. Avoid contact with eyes.

WHEN USING

• do not bandage tightly
• do not apply to wounds or damaged skin

Stop use and ask a doctor if

• condition worsens • symptoms persist for more than 7 days or clear up and occur again within a few days.

Keep out of reach of children. If swallowed, get medical help or contact a Poison Control Center right away

PREGNANCY OR BREAST FEEDING

If pregnant or breast-feeding, ask a health professional before use.

DOSAGE AND ADMINISTRATION

Adults and children 2 years of age and older: apply to affected area not more than 3 to 4 times daily. Children under 2 years of age: consult a doctor.

Other information

• do not freeze
• Keep lid tightly closed

INACTIVE INGREDIENT

Inactive ingredients carbomer, propylene glycol, methylparaben, isopropyl alcohol, triethanol- amine, FD&C Blue no. 1, purified water.

PACKAGE LABEL

227 g NDC: 69822-013-80

MMM Therapeutic Ice Gel

Topical Analgesic

Net Wt. 8 oz